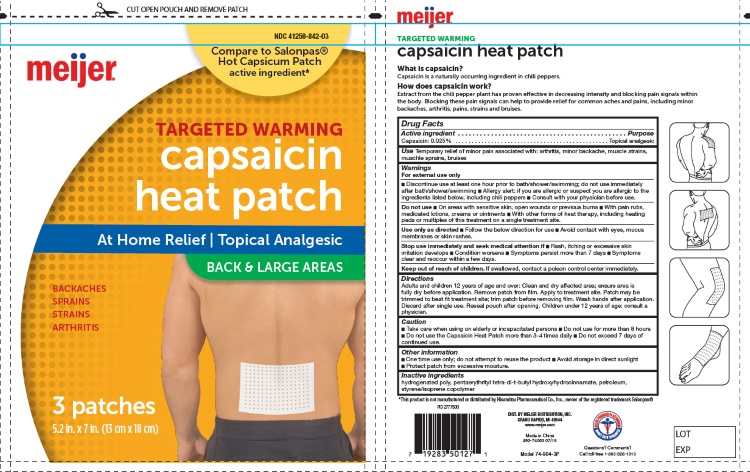 DRUG LABEL: CAPSAICIN  HEAT PATCHES BACK AND LARGE AREAS
NDC: 41250-842 | Form: PATCH
Manufacturer: Meijer Distribution Inc
Category: otc | Type: HUMAN OTC DRUG LABEL
Date: 20260126

ACTIVE INGREDIENTS: CAPSAICIN 0.025 g/100 g
INACTIVE INGREDIENTS: PENTAERYTHRITOL TETRAKIS(3-(3,5-DI-TERT-BUTYL-4-HYDROXYPHENYL)PROPIONATE); HYDROGENATED POLYDECENE (550 MW); LIQUID PETROLEUM; STYRENE/ACRYLAMIDE COPOLYMER (MW 500000)

CAPSAICIN HEAT PATCH BACK AND LARGE AREAS

For External Use Only

- Discontinue use at least one hour prior to bath / shower / swimming; do not use immediatelty after bath / shower / swimming.
- Allergy alert: if you are allergic or suspect you are allergic to the ingredients listed below, including chili perppers.. consults with your physician before use.

Uses

Temporary relief of minor pain associated with:

- Arthiritis
- Minor backache
- Strains
- Sprains
- Bruises

Purpose

Temporary relief of minor pain associated with: arthritis, minor backache, muscle strains,
muschle sprains, bruises

Active Ingredients

Capsaicin: 0.025%...........................Topical Analgesic

Inactive Ingredients:

Hydrogenated Poly, Pentaerythrityl Tetra-di-t-butyl Hydroxyhydrocinnamate, Petroleum, Styrene / Isoprene Copolymer

Directions for Use:

For Use on Adults and Childrens 12 Years of Age or Older

- Clean and dru affected area; ensure area is fully dry before application
- Remove patch from film
- Apply to treatement site
- Patch may be trimmerd to best fit treatment site; trim patch before removing film
- Wash hands after application
- Discard after signle use

Caution:

- Take care when using on elderly ot incapacited persons
- Do not use more than 8 hours
- Do not use the Capsaicin Heat Patch more than 3-4 times daily
- Do not exceed 7 days of continue use

Keep Out of Reach of Children

if swallowed, contact a poison control center immediately.

Storage and Care:

- One time use only; do not attempt to reuse the product
- avoid storage in direct sunlight
- Protect patch from excessive moisture

Do Not Use:

- On areas with sensitive skin, open wounds or previous burns
- with pain rubs, medicated lotions, creams or oinments
- with other forms of heat theraphy, including heating pads, or multiples of this treatment on a single treatement site

Use Only as Directed:

- Follow the below directions for use.
- Avoid contact with eyes, mucus membrances or skin rashes.

Stop Use immediately and Seek Medical Attention if:

- Rash, itching or excessive skin irritation develops
- Conditions worsens
- Symptons persist more than 7 days
- Symptoms clear, and reoccur within a few days

QUESTIONS

866-326-1313

LABEL

DIST. BY MEIJER DISTRIBUTION, INC.
GRAND RAPIDS, MI 49544
www.meijer.com

Made in China